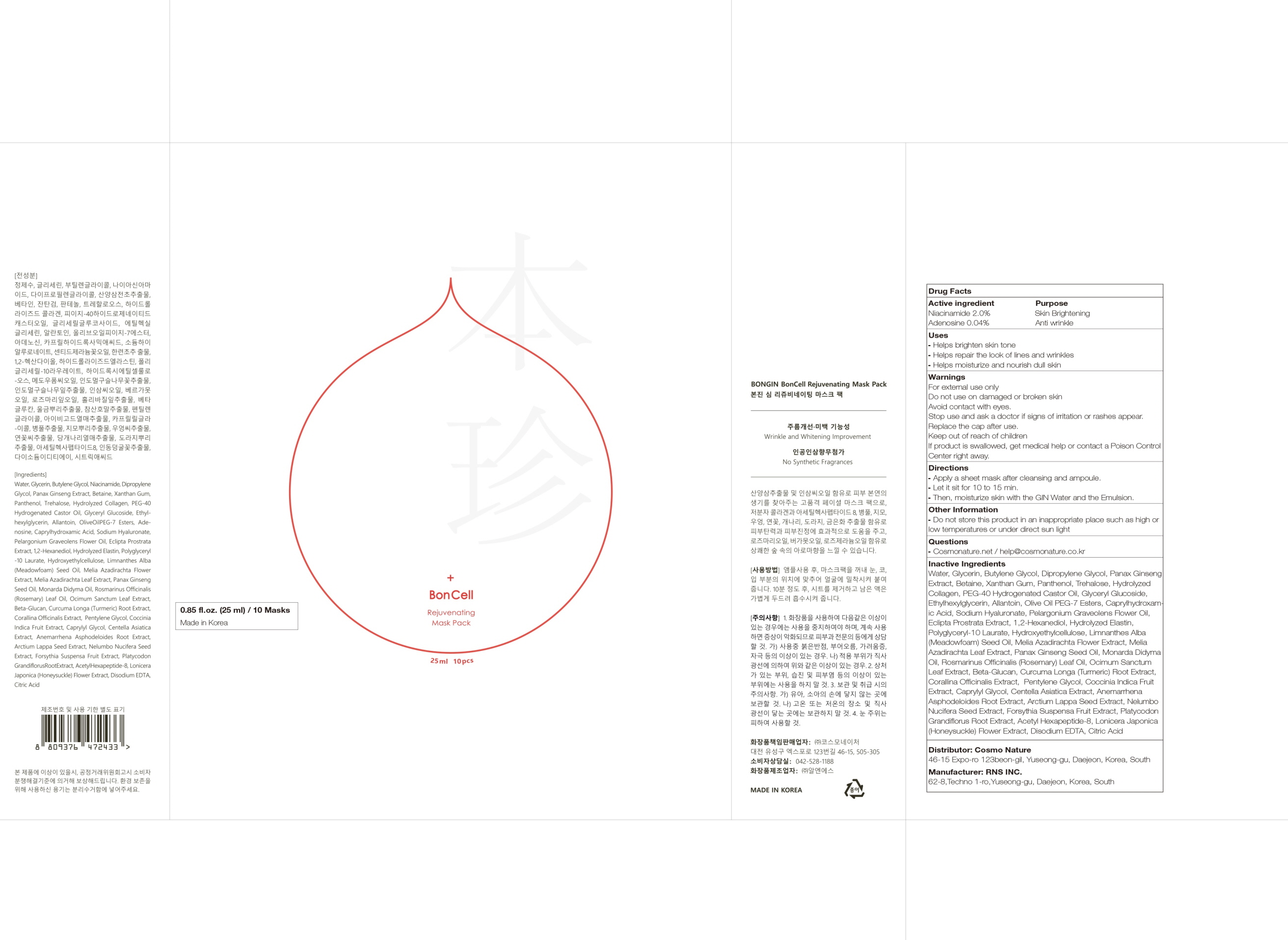 DRUG LABEL: BonGin BonCell Rejuvenating Mask Pack
NDC: 82492-040 | Form: PATCH
Manufacturer: Cosmo Nature
Category: otc | Type: HUMAN OTC DRUG LABEL
Date: 20231213

ACTIVE INGREDIENTS: Niacinamide 2.0 g/100 mL; Adenosine 0.04 g/100 mL
INACTIVE INGREDIENTS: Water; Glycerin; Butylene Glycol; Dipropylene Glycol; Betaine

ACTIVE INGREDIENTS

Niacinamide 2.0%
Adenosine 0.04%

INACTIVE INGREDIENTS

Water, Glycerin, Butylene Glycol, Dipropylene Glycol, Panax Ginseng Extract, Betaine, Xanthan Gum, Panthenol, Trehalose, Hydrolyzed Collagen, PEG-40 Hydrogenated Castor Oil, Glyceryl Glucoside, Ethylhexylglycerin, Allantoin, Olive Oil PEG-7 Esters, Caprylhydroxamic Acid, Sodium Hyaluronate, Pelargonium Graveolens Flower Oil, Eclipta Prostrata Extract, 1,2-Hexanediol, Hydrolyzed Elastin, Polyglyceryl-10 Laurate, Hydroxyethylcellulose, Limnanthes Alba (Meadowfoam) Seed Oil, Melia Azadirachta Flower Extract, Melia Azadirachta Leaf Extract, Panax Ginseng Seed Oil, Monarda Didyma Oil, Rosmarinus Officinalis (Rosemary) Leaf Oil, Ocimum Sanctum Leaf Extract, Beta-Glucan, Curcuma Longa (Turmeric) Root Extract, Corallina Officinalis Extract, Pentylene Glycol, Coccinia Indica Fruit Extract, Caprylyl Glycol, Centella Asiatica Extract, Anemarrhena Asphodeloides Root Extract, Arctium Lappa Seed Extract, Nelumbo Nucifera Seed Extract, Forsythia Suspensa Fruit Extract, Platycodon Grandiflorus Root Extract, Acetyl Hexapeptide-8, Lonicera Japonica (Honeysuckle) Flower Extract, Disodium EDTA, Citric Acid

PURPOSE

Skin Brightening
Anti wrinkle

WARNINGS

For external use only
Do not use on damaged or broken skin
Avoid contact with eyes.
Stop use and ask a doctor if signs of irritation or rashes appear.
Replace the cap after use.
Keep out of reach of children
If product is swallowed, get medical help or contact a Poison Control Center right away.

KEEP OUT OF REACH OF CHILDREN

Uses

■ Helps brighten skin tone
■ Helps repair the look of lines and wrinkles
■ Helps moisturize and nourish dull skin

Directions

■ Apply a sheet mask after cleansing and ampoule.
■ Let it sit for 10 to 15 min.
■ Then, moisturize skin with the GIN Water and the Emulsion.

Other Information

■ Do not store this product in an inappropriate place such as high or low temperatures or under direct sun light

Questions

■ Cosmonature.net / help@cosmonature.co.kr